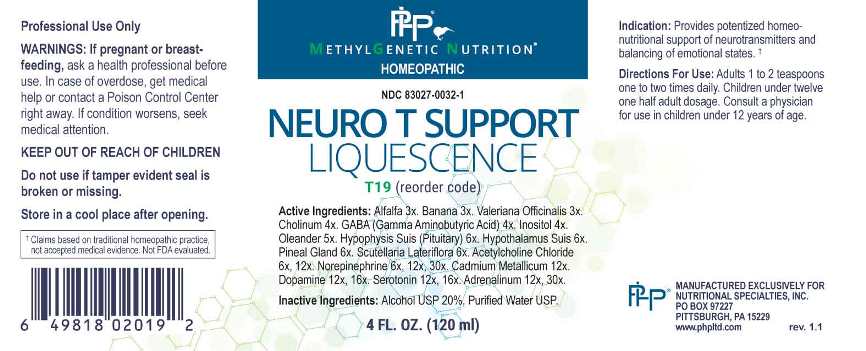 DRUG LABEL: Neuro T Support Liquescence
NDC: 83027-0032 | Form: LIQUID
Manufacturer: Nutritional Specialties, Inc.
Category: homeopathic | Type: HUMAN OTC DRUG LABEL
Date: 20230425

ACTIVE INGREDIENTS: MEDICAGO SATIVA WHOLE 3 [hp_X]/1 mL; BANANA 3 [hp_X]/1 mL; VALERIAN 3 [hp_X]/1 mL; CHOLINE HYDROXIDE 4 [hp_X]/1 mL; .GAMMA.-AMINOBUTYRIC ACID 4 [hp_X]/1 mL; INOSITOL 4 [hp_X]/1 mL; NERIUM OLEANDER LEAF 5 [hp_X]/1 mL; SUS SCROFA PITUITARY GLAND 6 [hp_X]/1 mL; SUS SCROFA HYPOTHALAMUS 6 [hp_X]/1 mL; SUS SCROFA PINEAL GLAND 6 [hp_X]/1 mL; SCUTELLARIA LATERIFLORA WHOLE 6 [hp_X]/1 mL; ACETYLCHOLINE CHLORIDE 6 [hp_X]/1 mL; NOREPINEPHRINE BITARTRATE 6 [hp_X]/1 mL; CADMIUM 12 [hp_X]/1 mL; DOPAMINE HYDROCHLORIDE 12 [hp_X]/1 mL; SEROTONIN HYDROCHLORIDE 12 [hp_X]/1 mL; EPINEPHRINE 12 [hp_X]/1 mL
INACTIVE INGREDIENTS: WATER; ALCOHOL

DRUG FACTS:

ACTIVE INGREDIENTS:

Alfalfa 3X, Banana 3X, Valeriana Officinalis 3X, Cholinum 4X, Gaba (Gamma Aminobutyric Acid) 4X, Inositol 4X, Oleander 5X, Hypophysis Suis 6X, Hypothalamus Suis (Pituitary 6X, Pineal Gland 6X, Scutellaria Lateriflora 6X, Acetylcholine Chloride 6X, 12X, Norepinephrine 6X, 12X, 30X, Cadmium Metallicum 12X, Dopamine 12X, 16X, Serotonin 12X, 16X, Adrenalinum 12X, 30X.

PURPOSE:

Provides potentized homeo-nutritional support of neurotransmitters and balancing of emotional states.†

†Claims based on traditional homeopathic practice, not accepted medical evidence. Not FDA evaluated.

WARNINGS:

Professional Use Only

If pregnant or breast-feeding, ask a health professional before use.

In case of overdose, get medical help or contact a Poison Control Center right away.

If condition worsens, seek medical attention.

KEEP OUT OF REACH OF CHILDREN

Do not use if tamper evident seal is broken or missing.

Store in a cool place after opening

KEEP OUT OF REACH OF CHILDREN:

In case of overdose, get medical help or contact a Poison Control Center right away.

DIRECTIONS:

Adults 1 to 2 teaspoons one to two times daily. Children under twelve one half adult dosage. Consult a physician for use in children under 12 years of age.

INDICATIONS:

Provides potentized homeo-nutritional support of neurotransmitters and balancing of emotional states.†

†Claims based on traditional homeopathic practice, not accepted medical evidence. Not FDA evaluated.

INACTIVE INGREDIENTS:

Alcohol USP 20%, Purified Water USP.

QUESTIONS:

MANUFACTURED EXCLUSIVELY FOR

NUTRITIONAL SPECIALTIES, INC.

PO BOX 97227

PITTSBURG, PA 15229

www.phpltd.com

PACKAGE LABEL DISPLAY:

METHYLGENETIC NUTRITION

HOMEOPATHIC

NDC 83027-0032-1

NEURO T SUPPORT

LIQUESCENCE

4 FL. OZ (120 ml)